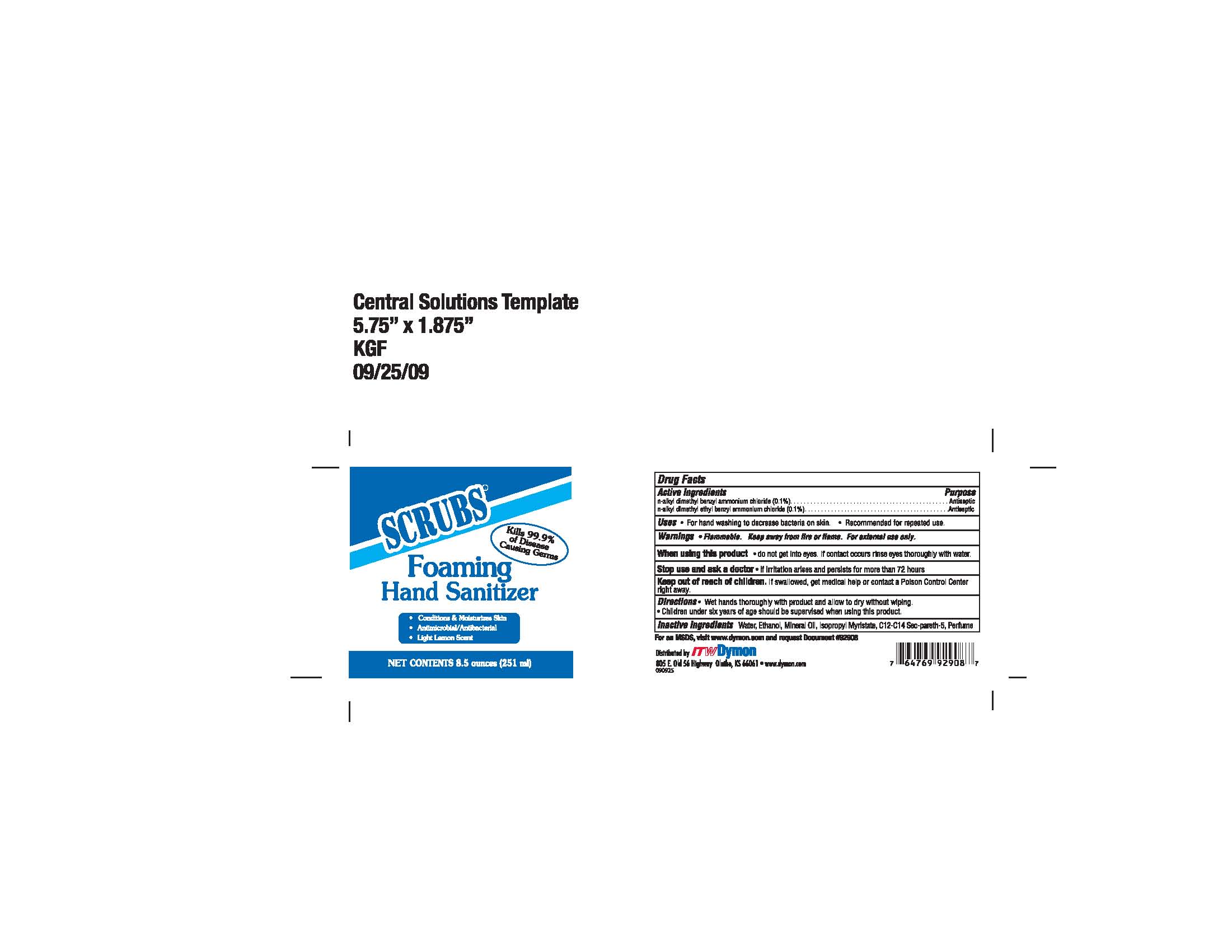 DRUG LABEL: SCRUBS Foaming Hand Sanitizer
NDC: 51239-1929 | Form: SOLUTION
Manufacturer: ITW Dymon
Category: otc | Type: HUMAN OTC DRUG LABEL
Date: 20091021

ACTIVE INGREDIENTS: BENZETHONIUM CHLORIDE 0.1 g/970 mL; BENZALKONIUM CHLORIDE 0.1 g/970 mL
INACTIVE INGREDIENTS: Mineral Oil 0.7 g/970 mL; Isopropyl Myristate 0.3 g/970 mL; Alcohol 20 g/970 mL; Water 78.02 g/970 mL

Active Ingredients Purpose

n-alkyl dimethyl benzyl ammonium chloride (0.1%)....................................Antiseptic

n-alkyl dimethyl ethyl benzyl ammonium chloride (0.1%)..........................Antiseptic

Stop use and ask a doctor

- if irritation arises and persists for more than 72 hours

Keep out of reach of children. If swallowed, get medical help or contact a Poison Control Center right away.

When using this product

- do not get into eyes. If contact occurs rinse eyes thoroughly with water.

Uses

- For hand washing to decrease bacteria on skin.
- Recommended for repeated use.

Directions

- Wet hands thoroughly with product and allow to dry without wiping.
- Children under six years of age should be supervised when using this product.

Warnings
Flammable, keep away from heat and flame.
For external use only.

QUESTIONS

Inactive Ingredients
Water, ethanol, Mineral Oil, Isoproply Myristate, C12-C14 Sec-pareth-5